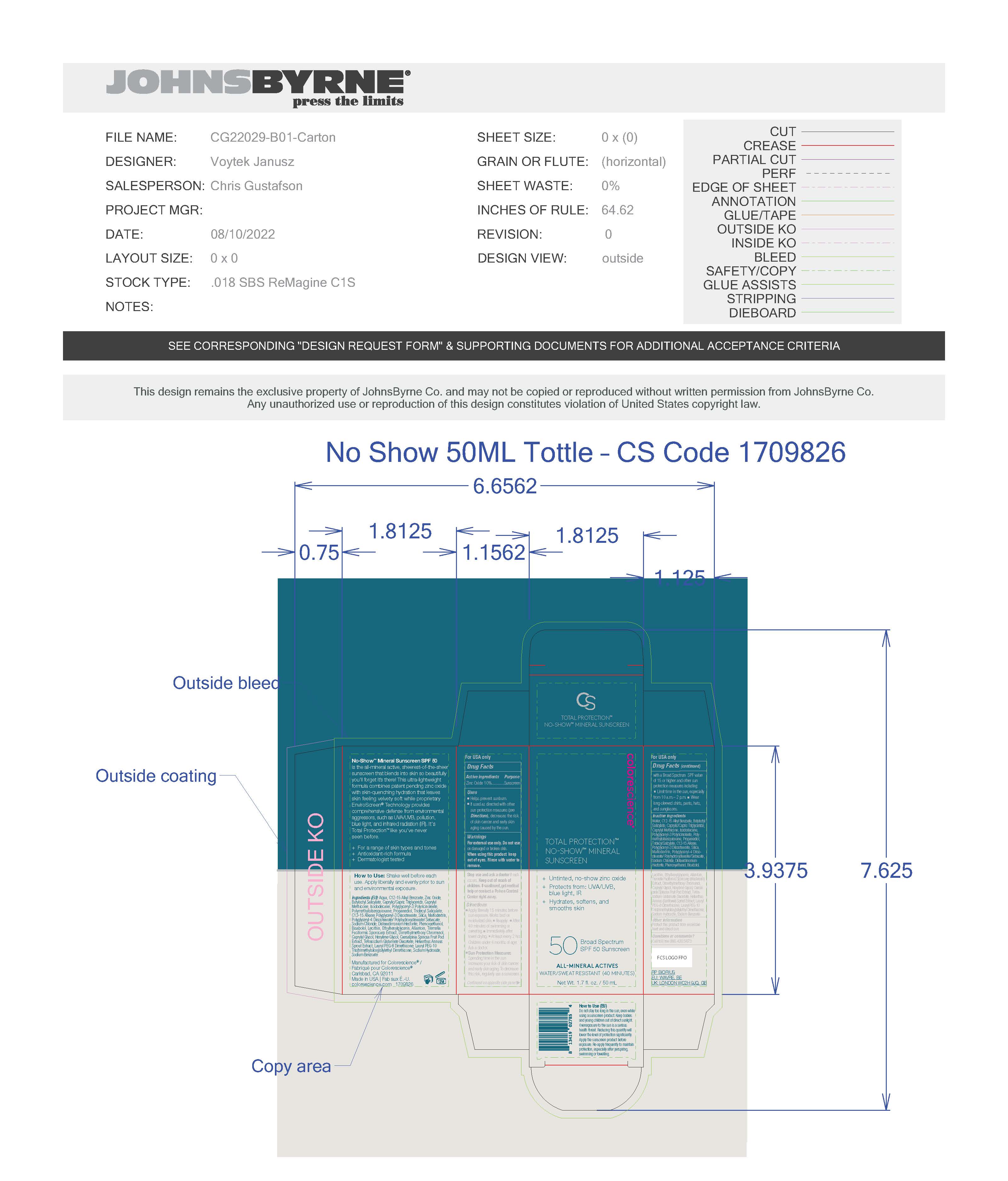 DRUG LABEL: Colorescience Total Protection No Show Mineral Sunscreen
NDC: 68078-066 | Form: LOTION
Manufacturer: Colorescience
Category: otc | Type: HUMAN OTC DRUG LABEL
Date: 20251015

ACTIVE INGREDIENTS: ZINC OXIDE 107 mg/1 mL
INACTIVE INGREDIENTS: LAURYL PEG-8 DIMETHICONE (300 CPS); POLYGLYCERYL-3 DIISOSTEARATE; BUTYLOCTYL SALICYLATE; DIMETHYLMETHOXY CHROMANOL; DISTEARDIMONIUM HECTORITE; HEXYLENE GLYCOL; POLYGLYCERYL-2 DIPOLYHYDROXYSTEARATE; TRIDECYL SALICYLATE; PHENOXYETHANOL; MALTODEXTRIN; ETHYLHEXYLGLYCERIN; ALLANTOIN; TREMELLA FUCIFORMIS FRUITING BODY; SODIUM HYDROXIDE; WATER; PROPANEDIOL; TETRASODIUM GLUTAMATE DIACETATE; SODIUM CHLORIDE; ALKYL (C12-15) BENZOATE; CAESALPINIA SPINOSA FRUIT POD; HELIANTHUS ANNUUS SPROUT; SILICON DIOXIDE; ISODODECANE; POLYMETHYLSILSESQUIOXANE (11 MICRONS); .ALPHA.-BISABOLOL, (+)-

Colorescience Total Protection No Show Mineral Sunscreen